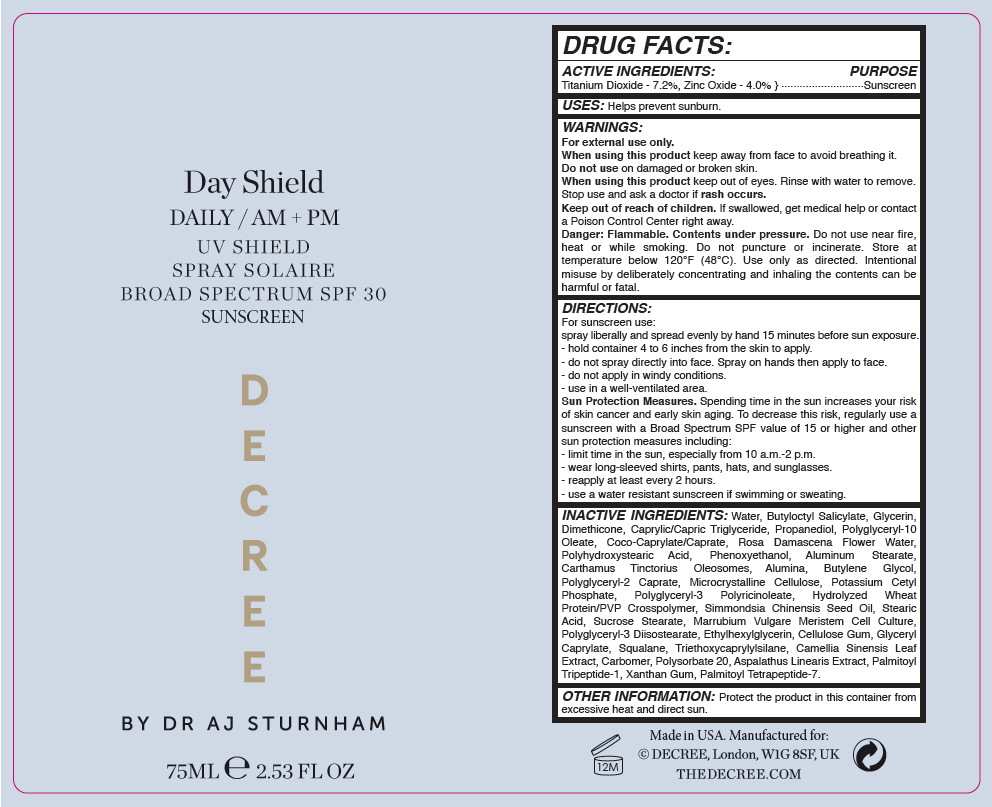 DRUG LABEL: Decree Daily Shield Broad Spectrum SPF 30 Sunscreen
NDC: 66163-3919 | Form: LIQUID
Manufacturer: Cosmetic Solutions LLC
Category: otc | Type: HUMAN OTC DRUG LABEL
Date: 20220404

ACTIVE INGREDIENTS: Titanium Dioxide 7.2 g/100 mL; Zinc Oxide 4 g/100 mL
INACTIVE INGREDIENTS: WATER; BUTYLOCTYL SALICYLATE; GLYCERIN; DIMETHICONE; MEDIUM-CHAIN TRIGLYCERIDES; PROPANEDIOL; POLYGLYCERYL-10 OLEATE; COCOYL CAPRYLOCAPRATE; ROSA X DAMASCENA FLOWER OIL; PHENOXYETHANOL; ALUMINUM STEARATE; CARTHAMUS TINCTORIUS SEED OLEOSOMES; ALUMINUM OXIDE; BUTYLENE GLYCOL; POLYGLYCERYL-2 CAPRATE; MICROCRYSTALLINE CELLULOSE; POTASSIUM CETYL PHOSPHATE; POLYGLYCERYL-3 PENTARICINOLEATE; JOJOBA OIL; STEARIC ACID; SUCROSE STEARATE; POLYGLYCERYL-3 DIISOSTEARATE; ETHYLHEXYLGLYCERIN; CARBOXYMETHYLCELLULOSE SODIUM, UNSPECIFIED; GLYCERYL MONOCAPRYLATE; SQUALANE; TRIETHOXYCAPRYLYLSILANE; GREEN TEA LEAF; CARBOMER HOMOPOLYMER, UNSPECIFIED TYPE; POLYSORBATE 20; PALMITOYL TRIPEPTIDE-1; XANTHAN GUM; PALMITOYL TETRAPEPTIDE-7

Decree Daily Shield Broad Spectrum SPF 30 Sunscreen

DRUG FACTS:

ACTIVE INGREDIENTS

Titanium Dioxide - 7.2%, Zinc Oxide - 4.0%

PURPOSE

Sunscreen

USES

Helps prevent sunburn.

WARNINGS

For external use only.

When using this product keep away from face to avoid breathing it.

Do not use on damaged or broken skin.

When using this product keep out of eyes. Rinse with water to remove.

Stop use and ask a doctor if rash occurs.

Keep out of reach of children. If swallowed, get medical help or contact a Poison Control Center right away.

Danger

Flammable. Contents under pressure. Do not use near fire, heat or while smoking. Do not puncture or incinerate. Store at temperature below 120°F (48°C). Use only as directed. Intentional misuse by deliberately concentrating and inhaling the contents can be harmful or fatal.

DIRECTIONS

For sunscreen use:

spray liberally and spread evenly by hand 15 minutes before sun exposure.

- hold container 4 to 6 inches from the skin to apply.
- do not spray directly into face. Spray on hands then apply to face.
- do not apply in windy conditions.
- use in a well-ventilated area.

Sun Protection Measures

Spending time in the sun increases your risk of skin cancer and early skin aging. To decrease this risk, regularly use a sunscreen with a Broad Spectrum SPF value of 15 or higher and other sun protection measures including:

- limit time in the sun, especially from 10 a.m.-2 p.m.
- wear long-sleeved shirts, pants, hats, and sunglasses.
- reapply at least every 2 hours.
- use a water resistant sunscreen if swimming or sweating.

INACTIVE INGREDIENTS

Water, Butyloctyl Salicylate, Glycerin, Dimethicone, Caprylic/Capric Triglyceride, Propanediol, Polyglyceryl-10 Oleate, Coco-Caprylate/Caprate, Rosa Damascena Flower Water, Polyhydroxystearic Acid, Phenoxyethanol, Aluminum Stearate, Carthamus Tinctorius Oleosomes, Alumina, Butylene Glycol, Polyglyceryl-2 Caprate, Microcrystalline Cellulose, Potassium Cetyl Phosphate, Polyglyceryl-3 Polyricinoleate, Hydrolyzed Wheat Protein/PVP Crosspolymer, Simmondsia Chinensis Seed Oil, Stearic Acid, Sucrose Stearate, Marrubium Vulgare Meristem Cell Culture, Polyglyceryl-3 Diisostearate, Ethylhexylglycerin, Cellulose Gum, Glyceryl Caprylate, Squalane, Triethoxycaprylylsilane, Camellia Sinensis Leaf Extract, Carbomer, Polysorbate 20, Aspalathus Linearis Extract, Palmitoyl Tripeptide-1, Xanthan Gum, Palmitoyl Tetrapeptide-7.

OTHER INFORMATION

Protect the product in this container from excessive heat and direct sun.

PRINCIPAL DISPLAY PANEL - 75 ML Can Label

Day Shield
DAILY / AM + PM
UV SHIELD
SPRAY SOLAIRE
BROAD SPECTRUM SPF 30
SUNSCREEN

D
E
C
R
E
E

BY DR AJ STURNHAM

75ML e 2.53 FL OZ